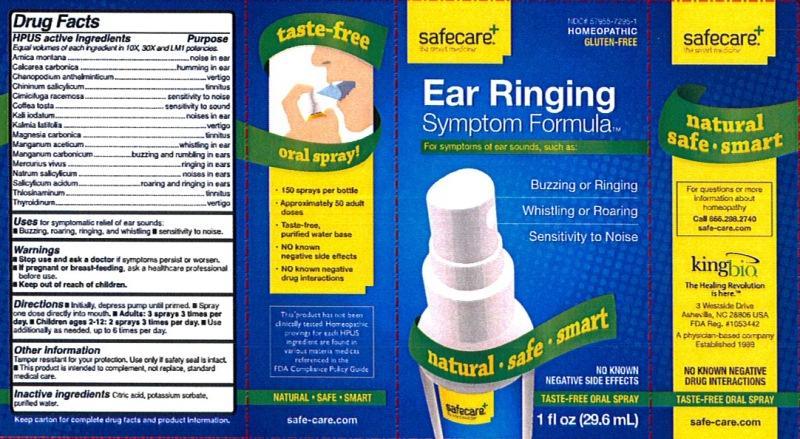 DRUG LABEL: Ear Ringing Symptom Formula
NDC: 57955-7295 | Form: LIQUID
Manufacturer: King Bio Inc.
Category: homeopathic | Type: HUMAN OTC DRUG LABEL
Date: 20131209

ACTIVE INGREDIENTS: ARNICA MONTANA 10 [hp_X]/29.6 mL; OYSTER SHELL CALCIUM CARBONATE, CRUDE 10 [hp_X]/29.6 mL; DYSPHANIA AMBROSIOIDES 10 [hp_X]/29.6 mL; QUININE SALICYLATE 10 [hp_X]/29.6 mL; BLACK COHOSH 10 [hp_X]/29.6 mL; COFFEA ARABICA SEED, ROASTED 10 [hp_X]/29.6 mL; POTASSIUM IODIDE 10 [hp_X]/29.6 mL; KALMIA LATIFOLIA LEAF 10 [hp_X]/29.6 mL; MAGNESIUM CARBONATE 10 [hp_X]/29.6 mL; MANGANESE ACETATE TETRAHYDRATE 10 [hp_X]/29.6 mL; MANGANESE CARBONATE 10 [hp_X]/29.6 mL; MERCURY 10 [hp_X]/29.6 mL; SODIUM SALICYLATE 10 [hp_X]/29.6 mL; SALICYLIC ACID 10 [hp_X]/29.6 mL; ALLYLTHIOUREA 10 [hp_X]/29.6 mL; THYROID, UNSPECIFIED 10 [hp_X]/29.6 mL
INACTIVE INGREDIENTS: WATER; CITRIC ACID MONOHYDRATE; POTASSIUM SORBATE

Ear Ringing Symptom Formula™

Drug Facts

____________________________________________________________________________________________________________

Equal volumes of each ingredient in 10X, 30X, and LM1 potencies.

HPUS active ingredients: Arnica montana, Calcarea carbonica, Chenopodium anthelminticum, Chininum salicylicum, Cimicifuga racemosa, Coffea tosta, Kali iodatum, Kalmia latifolia, Magnesia carbonica, Manganum aceticum, Manganum carbonicum, Mercurius vivus, Natrum salicylicum, Salicylicum acidum, Thiosinaminum, Thyroidinum.

INDICATIONS AND USAGE

Uses for symptomic relief of ear sounds:

- buzzing, roaring, ringing, and whistling
- sensitivity to noise

Warnings

- Stop use and ask a doctor if symptoms persist or worsen.
- If pregnant or breast-feeding, ask a healthcare professional before use.

- Keep out of reach of children.

Directions:

- Initially, depress pump until primed.
- Spray one dose directly into mouth.
- Adults: 3 sprays 3 times per day.
- Children 6-12 years: 2 sprays 3 times per day.
- Use additionally as needed, up to 6 times per day.

OTHER SAFETY INFORMATION

- Tamper resistant for your protection. Use only if safety seal is intact.
- This product is intended to complement, not replace, standard medical care.

INACTIVE INGREDIENT

Inactive Ingredients: Bio-Energetically Enhanced pure water, citric acid and potassium sorbate.

PURPOSE

Drug Facts __________________________________________________________________________________________________________________ HPUS active ingredients Purpose

Equal volumes of each ingredient in 10X, 30X, and LM1 potencies.

Arnica montana.....................................................................noise in ear

Calcarea carbonica.................................................................humming in ear

Chenopodium anthelminticum..................................................vertigo

Chininum salicylicum..............................................................tinnitus

Cimicifuga racemosa...............................................................sensitivity to noise

Coffea tosta...........................................................................sensitivity to sound

Kali iodatum..........................................................................noises in ear

Kalmia latifolia.......................................................................vertigo

Magnesia carbonica.................................................................tinnitus

Manganum aceticum...............................................................whistling in ear

Manganum carbonicum...........................................................buzzing and rumbling in ears

Mercurius vivus......................................................................ringing in ears

Natrum salicylicum.................................................................noises in ears

Salicylicum acidum.................................................................roaring and ringing in ears

Thiosinaminum......................................................................tinnitus

Thyroidinum..........................................................................vertigo